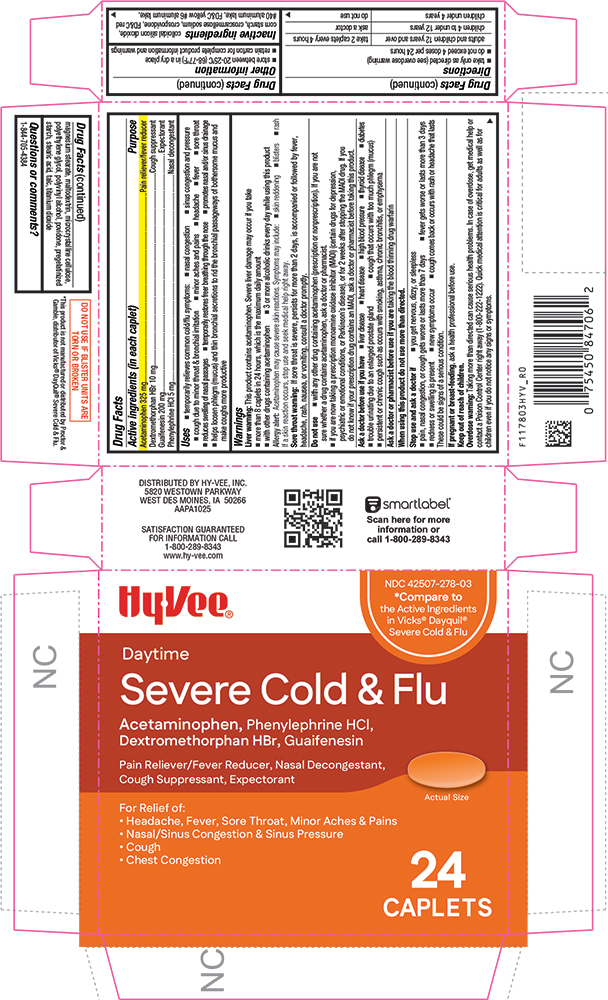 DRUG LABEL: Severe Cold and Flu
NDC: 42507-278 | Form: TABLET, COATED
Manufacturer: HYVEE INC
Category: otc | Type: HUMAN OTC DRUG LABEL
Date: 20260113

ACTIVE INGREDIENTS: ACETAMINOPHEN 325 mg/1 1; DEXTROMETHORPHAN HYDROBROMIDE 10 mg/1 1; GUAIFENESIN 200 mg/1 1; PHENYLEPHRINE HYDROCHLORIDE 5 mg/1 1
INACTIVE INGREDIENTS: SILICON DIOXIDE; CROSCARMELLOSE SODIUM; CROSPOVIDONE; FD&C RED NO. 40; ALUMINUM OXIDE; FD&C YELLOW NO. 6; MAGNESIUM STEARATE; MALTODEXTRIN; CELLULOSE, MICROCRYSTALLINE; POLYETHYLENE GLYCOL, UNSPECIFIED; POLYVINYL ALCOHOL; POVIDONE; STARCH, PREGELATINIZED CORN; STEARIC ACID; TALC; TITANIUM DIOXIDE

1178-HYV-2026-0113

Drug Facts

ACTIVE INGREDIENT

Active ingredients (in each caplet) | Purpose
Acetaminophen 325 mg | Pain reliever/fever reducer
Dextromethorphan HBr 10 mg | Cough suppressant
Guaifenesin 200 mg | Expectorant
Phenylephrine HCl 5 mg | Nasal decongestant

Uses

- temporarily relieves common cold/flu symptoms:
  - nasal congestion
  - sinus congestion and pressure
  - cough due to minor throat & bronchial irritation
  - minor aches and pains
  - headache
  - fever
  - sore throat
- reduces swelling of nasal passages
- temporarily restores freer breathing through the nose
- promotes nasal and/or sinus drainage
- helps loosen phlegm (mucus) and thin bronchial secretions to rid the bronchial passageways of bothersome mucus and make coughs more productive

Warnings

Liver warning

This product contains acetaminophen. Severe liver damage may occur if you take

- more than 8 caplets in 24 hours, which is the maximum daily amount
- with other drugs containing acetaminophen
- 3 or more alcoholic drinks every day while using this product

Allergy alert

Acetaminophen may cause severe skin reactions. Symptoms may include:

- skin reddening
- blisters
- rash

If a skin reaction occurs, stop use and seek medical help right away.

Sore throat warning

If sore throat is severe, persists for more than 2 days, is accompanied or followed by fever, headache, rash, nausea, or vomiting, consult a doctor promptly.

Do not use

- with any other drug containing acetaminophen (prescription or nonprescription). If you are not sure whether a drug contains acetaminophen, ask a doctor or pharmacist.
- if you are now taking a prescription monoamine oxidase inhibitor (MAOI) (certain drugs for depression, psychiatric, or emotional conditions, or Parkinson's disease), or for 2 weeks after stopping the MAOI drug. If you do not know if your prescription drug contains an MAOI, ask a doctor or pharmacist before taking this product.

Ask a doctor before use if you have

- liver disease
- heart disease
- high blood pressure
- thyroid disease
- diabetes
- trouble urinating due to an enlarged prostate gland
- cough that occurs with too much phlegm (mucus)
- persistent or chronic cough such as occurs with smoking, asthma, chronic bronchitis, or emphysema

Ask a doctor or pharmacist before use if you aretaking the blood thinning drug warfarin

When using this product do not use more than directed.

Stop use and ask a doctor if

- you get nervous, dizzy, or sleepless
- pain, nasal congestion, or cough gets worse or lasts more than 7 days
- fever gets worse or lasts more than 3 days
- redness or swelling is present
- new symptoms occur
- cough comes back or occurs with rash or headache that lasts

These could be signs of a serious condition.

PREGNANCY OR BREAST FEEDING

If pregnant or breast-feeding,ask a health professional before use.

Keep out of reach of children.

Overdose warning

Taking more than directed can cause serious health problems. In case of overdose, get medical help or contact a Poison Control Center right away (1-800-222-1222). Quick medical attention is critical for adults as well as for children even if you do not notice any signs or symptoms.

Directions

- take only as directed (see overdose warning)
- do not exceed 4 doses per 24 hours

adults and children 12 years and over | take 2 caplets every 4 hours
children 4 to under 12 years | ask a doctor
children under 4 years | do not use

Other information

- store between 20-25°C (68-77°F) in a dry place
- retain carton for complete product information and warnings

Inactive ingredients

colloidal silicon dioxide, corn starch, croscarmellose sodium, crospovidone, FD&C red #40 aluminum lake, FD&C yellow #6 aluminum lake, magnesium stearate, maltodextrin, microcrystalline cellulose, polyethylene glycol, polyvinyl alcohol, povidone, pregelatinized starch, stearic acid, talc, titanium dioxide

Questions or comments?

1-844-705-4384

PRINCIPAL DISPLAY PANEL

HyVee®

NDC 42507-278-03

*Compare to the Active Ingredients in Vicks® Dayquil® Severe Cold & Flu

Daytime

Severe Cold & Flu

Acetaminophen, Phenylephrine HCl, Dextromethorphan HBr, Guaifenesin

Pain Reliever/Fever Reducer, Nasal Decongestant, Cough Suppressant, Expectorant

For Relief of:

• Headache, Fever, Sore Throat, Minor Aches & Pains

• Nasal/Sinus Congestion & Sinus Pressure

• Cough

• Chest Congestion

Actual Size

24 CAPLETS